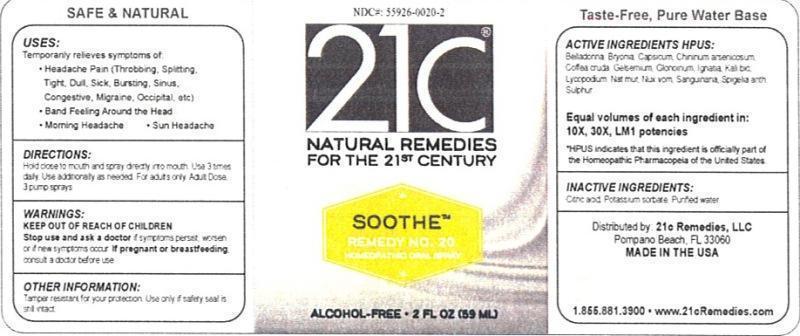 DRUG LABEL: Soothe Remedy No. 20
NDC: 55926-0020 | Form: LIQUID
Manufacturer: Speer Laboratories, LLC
Category: homeopathic | Type: HUMAN OTC DRUG LABEL
Date: 20130801

ACTIVE INGREDIENTS: ATROPA BELLADONNA 10 [hp_X]/59 mL; BRYONIA ALBA ROOT 10 [hp_X]/59 mL; CAPSICUM 10 [hp_X]/59 mL; QUININE ARSENITE 10 [hp_X]/59 mL; ARABICA COFFEE BEAN 10 [hp_X]/59 mL; GELSEMIUM SEMPERVIRENS ROOT 10 [hp_X]/59 mL; NITROGLYCERIN 10 [hp_X]/59 mL; STRYCHNOS IGNATII SEED 10 [hp_X]/59 mL; POTASSIUM DICHROMATE 10 [hp_X]/59 mL; LYCOPODIUM CLAVATUM SPORE 10 [hp_X]/59 mL; SODIUM CHLORIDE 10 [hp_X]/59 mL; STRYCHNOS NUX-VOMICA SEED 10 [hp_X]/59 mL; SANGUINARIA CANADENSIS ROOT 10 [hp_X]/59 mL; SPIGELIA ANTHELMIA 10 [hp_X]/59 mL; SULFUR 10 [hp_X]/59 mL
INACTIVE INGREDIENTS: WATER; CITRIC ACID MONOHYDRATE; POTASSIUM SORBATE

Soothe Remedy No. 20

ACTIVE INGREDIENT

Active Ingredients HPUS: Belladonna, Bryonia, Capsicum annuum, Chininum arsenicosum, Coffea cruda, Gelsemium sempervirens, Glonoinum, Ignatia amara, Kali bichromicum, Lycopodium clavatum, Natrum muriaticum, Nux vomica, Sanguinaria canadensis, Spigelia anthelmia, Sulphur.

Equal volumes of each ingredient in: 10X, 30X, LM1 potencies

HPUS indicates that this ingredient is officially part of the Homeopathic Pharmacopeia of the United States.

Inactive Ingredients: Citric acid, Potassium sorbate, Purified water.

INDICATIONS AND USAGE

Uses: Temporarily relieves symptoms of:

- headache pain (throbbing, splitting, tight, dull, sick, bursting, sinus, congestive, migraine, occiptal, etc)
- band feeling around the head
- morning headache
- sun headache

Directions:

Hold close to mouth and spray directly into mouth. Use 3 times daily. Use additionally as needed. For adults only. Adult dose 3 pump sprays.

Keep out of reach of children.

WARNINGS

Warnings: Stop use and ask a doctor if symptoms persist, worsen or if new symptoms occur. If pregnant or breastfeeding, consult a doctor before use.

OTHER SAFETY INFORMATION

Tamper resistant for your protection. Use only if safety seal is still intact.

PURPOSE

Uses: Temporarily relieves symptoms of: headache pain (throbbing, splitting, tight, dull, sick, bursting, sinus, congestive, migraine, occipital, etc), band feeling around the head, morning headache, sun headache.